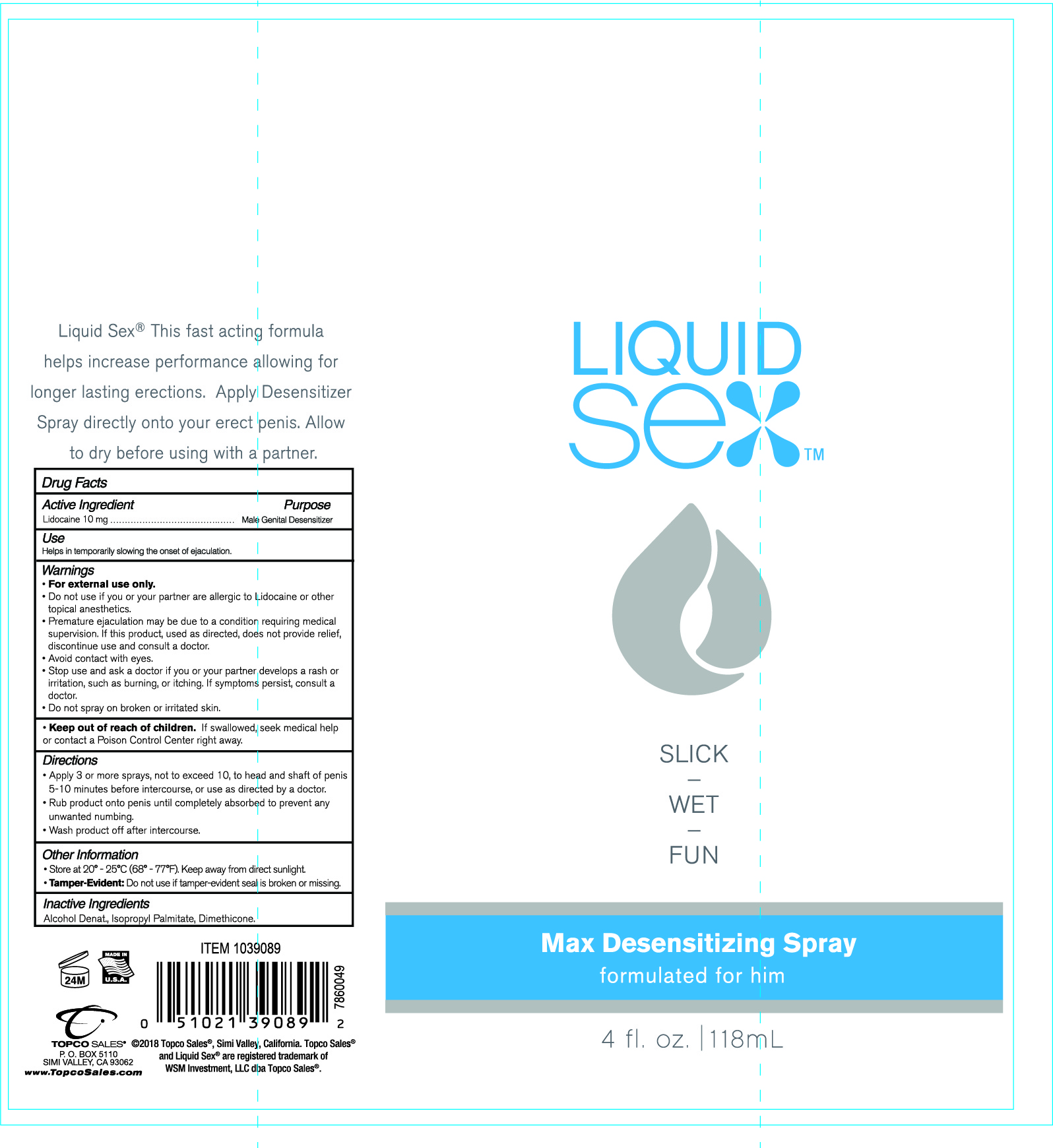 DRUG LABEL: Liquid Sex
NDC: 69797-100 | Form: SPRAY, METERED
Manufacturer: WSM Investment LLC. Topco Sales
Category: otc | Type: HUMAN OTC DRUG LABEL
Date: 20171117

ACTIVE INGREDIENTS: LIDOCAINE 10 mg/100 mL
INACTIVE INGREDIENTS: ISOPROPYL PALMITATE; ALCOHOL; DIMETHICONE

Active Ingredient

Lidocaine 10mg

PURPOSE

Male Genital Desensitizer

INDICATIONS AND USAGE

Helps in temporarily slowing the onset of ejaculation.

WARNINGS

- For external use only
- Do not use if you or your partner are allergic to Lidocaine or other topical anesthetics.
- Premature ejaculation may be due to a condition requiring medical supervision. If this product, used as directed, does not provide relief, discontinue use and consult a doctor.
- Avoid contact with eyes.
- Stop use and ask a doctor if you or your partner develops a rash or irritation, such as burning, or itching. If symptoms persist, consult a doctor.
- Do not spray on broken or irritated skin.

- Keep out of reach of children. If swallowed, seek medical help or contact a Posion Control Center right away.

DOSAGE AND ADMINISTRATION

- Apply 3 or more sprays, not to exceed 10, to head and shaft of penis 5-10 minutes before intercourse, or use as directed by a doctor.
- Rub product onto penis until completely absorbed to prevent any unwanted numbing.
- Wash product off after intercourse.

OTHER SAFETY INFORMATION

- Store at 20º - 25ºC (68º-77ºF). Keep away from direct sunlight.
- Tamper-Evident: Do not use if tamper-evident seal is broken or missing.

INACTIVE INGREDIENT

Alcohol Denat., Isopropyl Palmitate, Dimethicone.